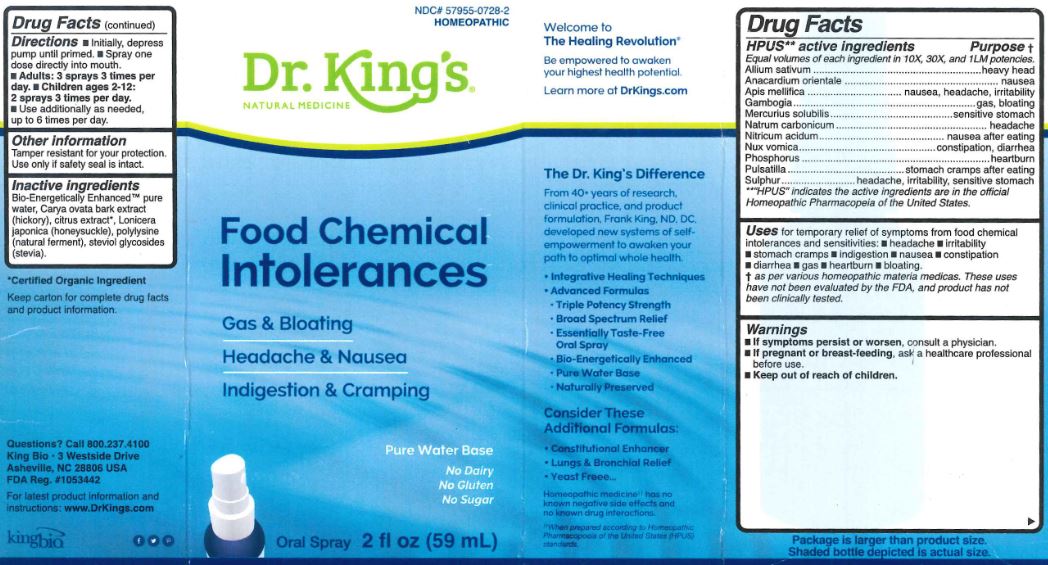 DRUG LABEL: Food Intolerances
NDC: 57955-0728 | Form: LIQUID
Manufacturer: King Bio Inc.
Category: homeopathic | Type: HUMAN OTC DRUG LABEL
Date: 20180221

ACTIVE INGREDIENTS: GARLIC 10 [hp_X]/59 mL; SEMECARPUS ANACARDIUM JUICE 10 [hp_X]/59 mL; APIS MELLIFERA 10 [hp_X]/59 mL; GAMBOGE 10 [hp_X]/59 mL; MERCURIUS SOLUBILIS 10 [hp_X]/59 mL; SODIUM CARBONATE 10 [hp_X]/59 mL; NITRIC ACID 10 [hp_X]/59 mL; STRYCHNOS NUX-VOMICA SEED 10 [hp_X]/59 mL; PHOSPHORUS 10 [hp_X]/59 mL; ANEMONE PULSATILLA 10 [hp_X]/59 mL; SULFUR 10 [hp_X]/59 mL
INACTIVE INGREDIENTS: WATER; CARYA OVATA BARK; CITRUS BIOFLAVONOIDS; LONICERA JAPONICA FLOWER; POLYEPSILON-LYSINE (4000 MW); REBAUDIOSIDE A

Food Chemical Intolerances™

ACTIVE INGREDIENT

Drug Facts__________________________________________________________________________________________________________

HPUS active ingredients: Allium sativum, Anacardium orientale, Apis Mellifica, Gambogia, Mercurius solubilis, Natrum carbonicum, Nitricum acidum, Nux vomica, Phosphorus, Pulsatilla, Sulphur

Equal volumes of each ingredient in 10X, 30X, and 1LM potencies.

INDICATIONS AND USAGE

Uses for temporary relief of symptoms from food chemical intolerances and sensitivities: headache, irritability, stomach cramps, indigestion, nausea, constipation, diarrhea, gas, heartburn, bloating.

Inactive Ingredients:

Bio-Energetically Enhanced™ pure water, Carya ovata bark extract (hickory), citrus extract, Lonicera japonica (honeysukle), polylysine (natural ferment), steviol glycosides (stevia).

Warnings

- If symptoms persist or worsen, consult a physician.
- If pregnant or breast-feeding, ask a healthcare professional before use.

- Keep out of reach of children.

Directions

- Initially, depress pump until primed.
- Spray one dose directly into mouth.
- Adults: 3 sprays 3 times per day.
- Children ages 2-12: 2 sprays 3 times per day.
- Use additionally as needed, up tp to 6 times per day.

OTHER SAFETY INFORMATION

Tamper resistant for your protection. Use only if safety seal is intact.

Purpose:

Allium sativum.....heavy head

Anacardium orientale......nausea

Apis Mellifica......nausea, headache, irritability

Gambogia........gas, boating

Mercurius solubilis.....sensitive stomach

Natrum carbonicum.....headache

Nitricum acidum....nausea after eating

Nux vomica....constipation, diarrhea

Phosphorus....heartburn

Pulsatilla.....stomach cramps after eating

Sulphur......headache, irritability, sensitive stomach